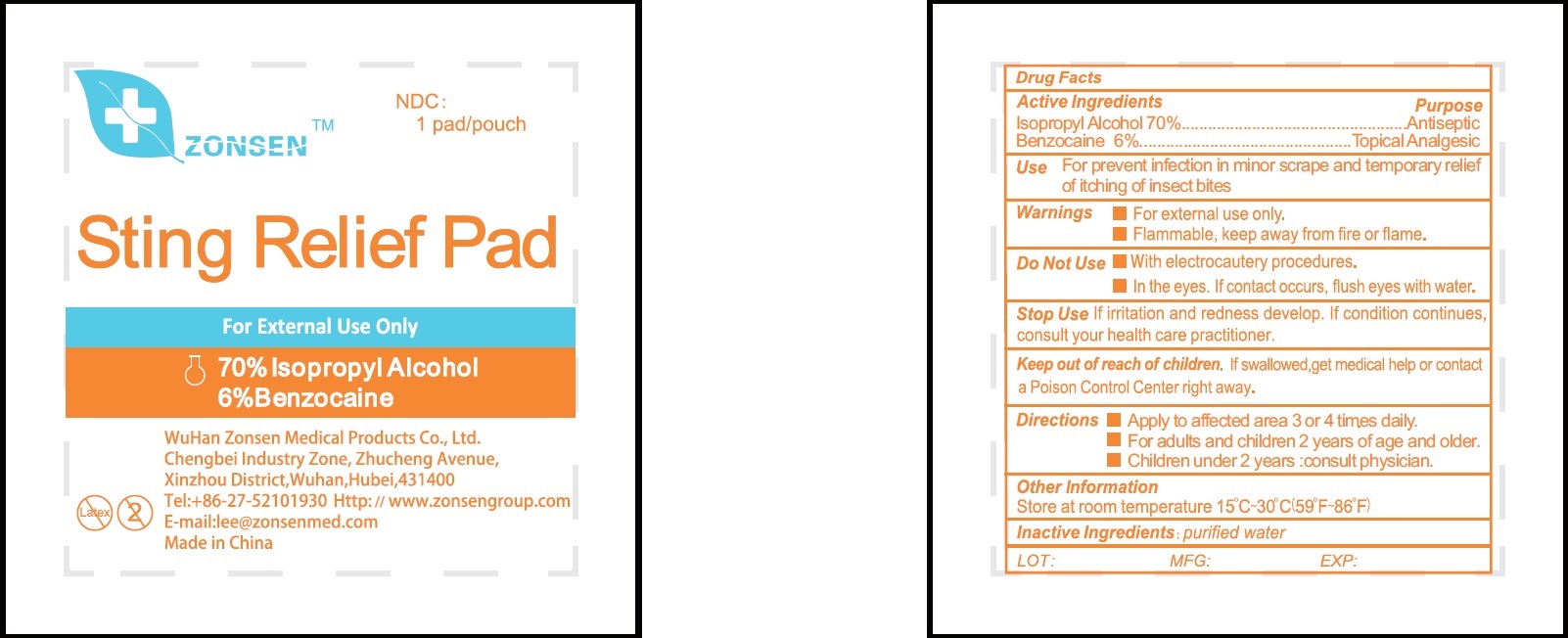 DRUG LABEL: Zonsen Sting Relief Pad
NDC: 72932-004 | Form: SWAB
Manufacturer: Wuhan Zonsen Medical Products Co., Ltd.
Category: otc | Type: HUMAN OTC DRUG LABEL
Date: 20190520

ACTIVE INGREDIENTS: ISOPROPYL ALCOHOL 0.7 mL/1 mL; BENZOCAINE 60 mg/1 mL
INACTIVE INGREDIENTS: WATER

Zonsen Sting Relief Pad

Active Ingredients

Isopropyl Alcohol 70%

Benzocaine 6%

Purpose

Antiseptic

Topical Analgesic

Use

For prevent infection in minor scrape and temporary relief of itching of insect bites

Warnings

- For external use only.
- Flammable, keep away from fire or flame.

Do Not Use

- With electrocautery procedures.
- In the eyes. If contact occurs, flush eyes with water.

Stop Use

if irritation and redness develop. If condition continues, consult your health care practitioner.

Keep out of reach of children.

If swallowed, get medical help or contact a Poison Control Center right away.

Directions

- Apply to affected area 3 or 4 times daily.
- For adults and children 2 years of age and older.
- Children under 2 years :consult physician.

Other information

Store at room temperature 15°C-30°C(59°F-86°F)

Inactive Ingredients:

purified water